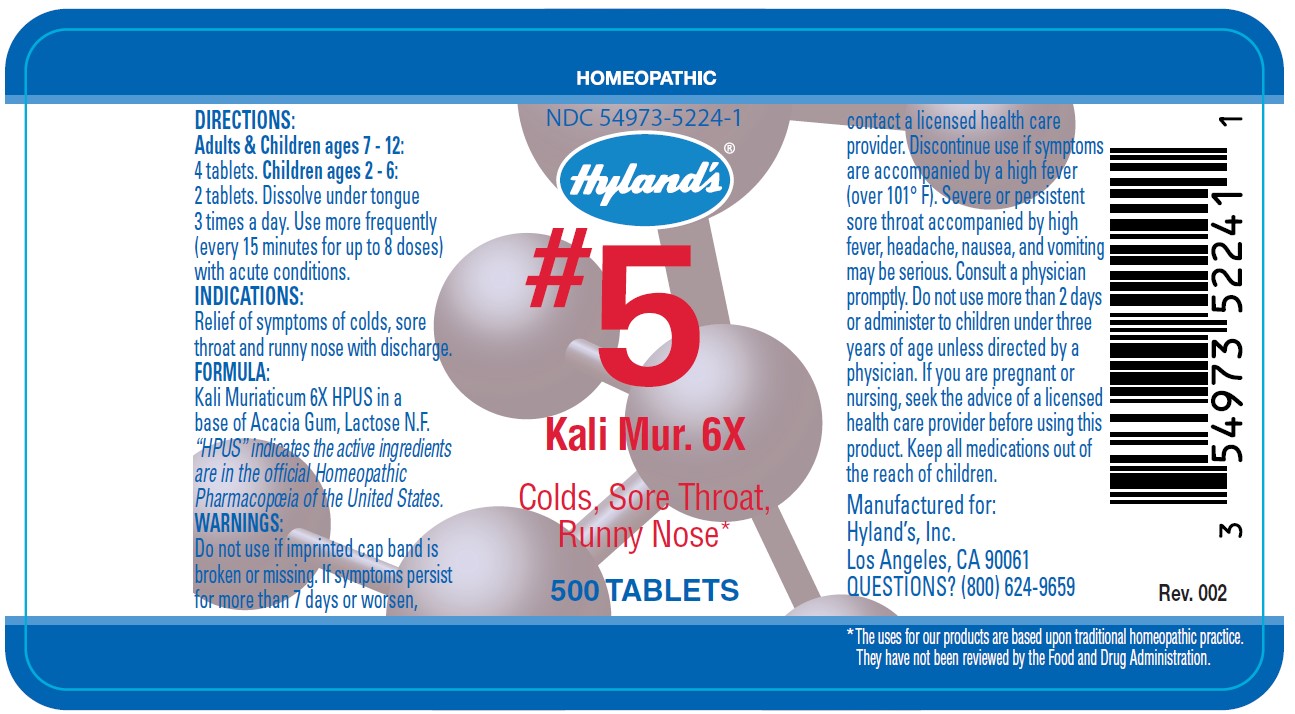 DRUG LABEL: KALI MURIATICUM
NDC: 54973-5224 | Form: TABLET
Manufacturer: Hyland's Inc.
Category: homeopathic | Type: HUMAN OTC DRUG LABEL
Date: 20221219

ACTIVE INGREDIENTS: POTASSIUM CHLORIDE 6 [hp_X]/1 1
INACTIVE INGREDIENTS: ACACIA; LACTOSE

#5 Kali Mur. 6X 500 Tablets

DIRECTIONS

Adults & Children ages 7 - 12: 4 tablets. Children ages 2 - 6: 2 tablets. Dissolve under tongue 3 times a day. Use more frequently (every 15 minutes for up to 8 doses) with acute conditions.

INDICATIONS

PURPOSE

Relief of symptoms of colds, sore throat and runny nose with a white discharge.

FORMULA

Kali Muriaticum 6X HPUS

INACTIVE INGREDIENT

In a base of Acacia Gum, Lactose N.F.

“HPUS” indicates that the active ingredients are in the official Homeopathic Pharmacopœia of the United States.

Warnings

Do not use if imprinted cap band is broken or missing.

ASK DOCTOR/PHARMACIST

If symptoms persist for more than seven days or worsen, contact a licensed health care provider.

STOP USE

Discontinue use if symptoms are accompanied by a high fever (over 101° F). Severe or persistent sore throat accompanied by high fever, headache, nausea, and vomiting may be serious. Consult physician promptly.

Do not use more than 2 days or administer to children under three years of age unless directed by physician.

PREGNANCY OR BREAST FEEDING

If you are pregnant or nursing, seek the advice of a licensed health care provider before using this product.

KEEP OUT OF REACH OF CHILDREN

Keep this and all medications out of the reach of children.

QUESTIONS?

(800) 624-9659

PRINCIPAL DISPLAY PANEL - 500 Tablet Bottle Label

HOMEOPATHIC

NDC 54973-5224-1

Hyland's

#5
Kali Mur. 6X

Colds, Sore Throat,
Runny Nose*

500 TABLETS